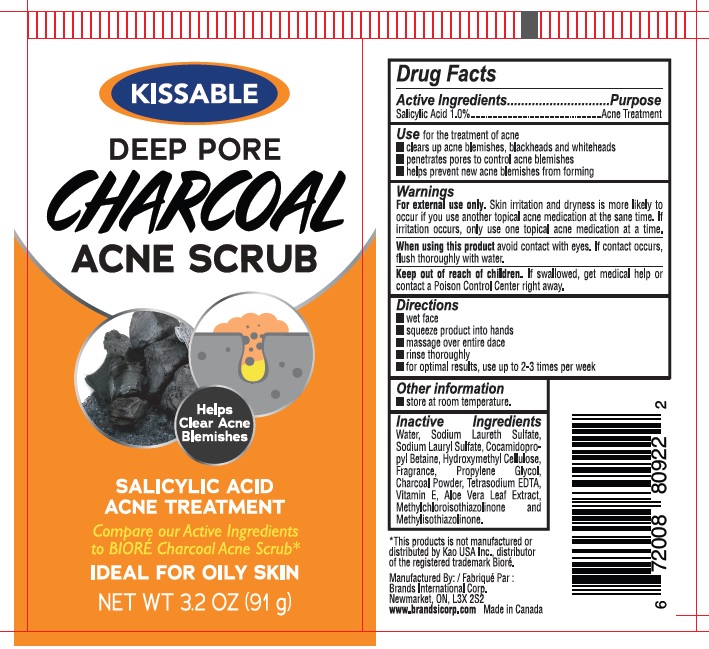 DRUG LABEL: Deep Pore Charcoal Acne scrub
NDC: 50157-013 | Form: LIQUID
Manufacturer: Brands International Corporation
Category: otc | Type: HUMAN OTC DRUG LABEL
Date: 20230227

ACTIVE INGREDIENTS: SALICYLIC ACID 1 g/100 mL
INACTIVE INGREDIENTS: PROPYLENE GLYCOL; WATER; SODIUM LAURETH SULFATE; COCAMIDOPROPYL BETAINE; SODIUM LAURYL SULFATE; HYDROXYMETHYL CELLULOSE; DITETRACYCLINE TETRASODIUM EDETATE; METHYLCHLOROISOTHIAZOLINONE; METHYLISOTHIAZOLINONE; BLACK WALNUT SHELL; VITAMIN E POLYETHYLENE GLYCOL SUCCINATE; ALOE VERA LEAF

KISSABLE - Deep Pore Charcoal Acne Scrub

ACTIVE INGREDIENT

Salicylic Acid 1.0%.

PURPOSE

Acne Treatment

DOSAGE AND ADMINISTRATION

Direction

Wet face

squeeze product into hands

massage over entire face

rinse thoroughly

for optimal results, use upto 2-3 times per week

Indications and Use

Clears up acme blemishes, blackheads and whitehaeads

penetrates pores to control acme blemishes

helps prevent new acme blemishes from forming

WARNINGS

For external use only

Avoid contact with eyes. If contact occurs, flush thoroughly with water

Stop use and ask a doctor if irritation or redness develops

When using this product

- skin irritation and dryness is more likely to occur if you use another topical acne medication at the same time
- if irritation occurs, only use one topical acne medication at a time.

Keep out of reach of children

In case of accidental ingestion, seek professional assistance or contact a poison control center immediately.

INACTIVE INGREDIENT

Water, Sodium Laureth Sulfate, Cocamidopropyl Betaine, Sodium Lauryl Sulfate, Hydroxymethyl cellulose, Fragrance, Tetrasodium EDTA, Methylchloroisothiazolinone, Methylisothiazolinone, Walnut Shell Powder, Vitamin E, Aloe Vera Leaf Extract.

OTHER SAFETY INFORMATION

Store at room temperature.